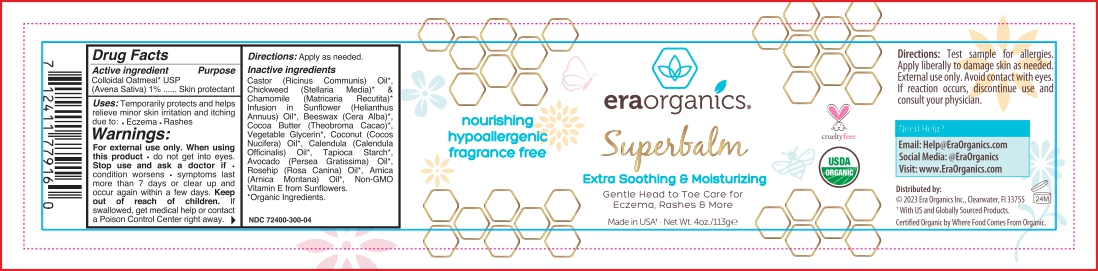 DRUG LABEL: Superbalm
NDC: 72400-300 | Form: SALVE
Manufacturer: Era Organics, Inc.
Category: otc | Type: HUMAN OTC DRUG LABEL
Date: 20251127

ACTIVE INGREDIENTS: OATMEAL 0.57 g/0.57 g

Superbalm Healing Ointment for Babies

Superbalm Healing Ointment for Babies

Colloidal Oatmeal 1%

Superbalm Healing Ointment for Babies

Castor (Ricinus Communis) Oil*, Chickweed (Stellaria Media)* & Chamomile (Matricaria Recutita)* Infusion in Sunflower (Helianthus Annuus) Oil*, Beeswax (Cera Alba), Cocoa Butter (Theobroma Cacao), Vegetable Glycerin*, Coconut (Cocos Nucifera) Oil*, Calendula (Calendula Officinalis) Flower Extract*, Tapioca Starch*, Avocado (Persea Gratissima) Oil*, Rosehip (Rosa Canina) Oil*, Arnica (Arnica Montana) Oil*, Non-GMO Vitamin E from Sunflowers*, Organic Ingredients.

Superbalm Healing Ointment for Babies

Skin Protectant

Superbalm Healing Ointment for Babies

Keep out of reach of children. If swallowed, get medical help or contact a Poison Control Center right away.

Superbalm Healing Ointment for Babies

Stop use and ask a doctor if condition worsens - symptoms last more than 7 days or clear up and occur again within a few days.

Superbalm Healing Ointment for Babies

Apply as needed.

Superbalm Healing Ointment for Babies

Temporarily protects and helps relieve minor skin irritation and itching due to: Eczema - Rashes

Superbalm Healing Ointment for Babies

For external use only. When using this product do not get into eyes